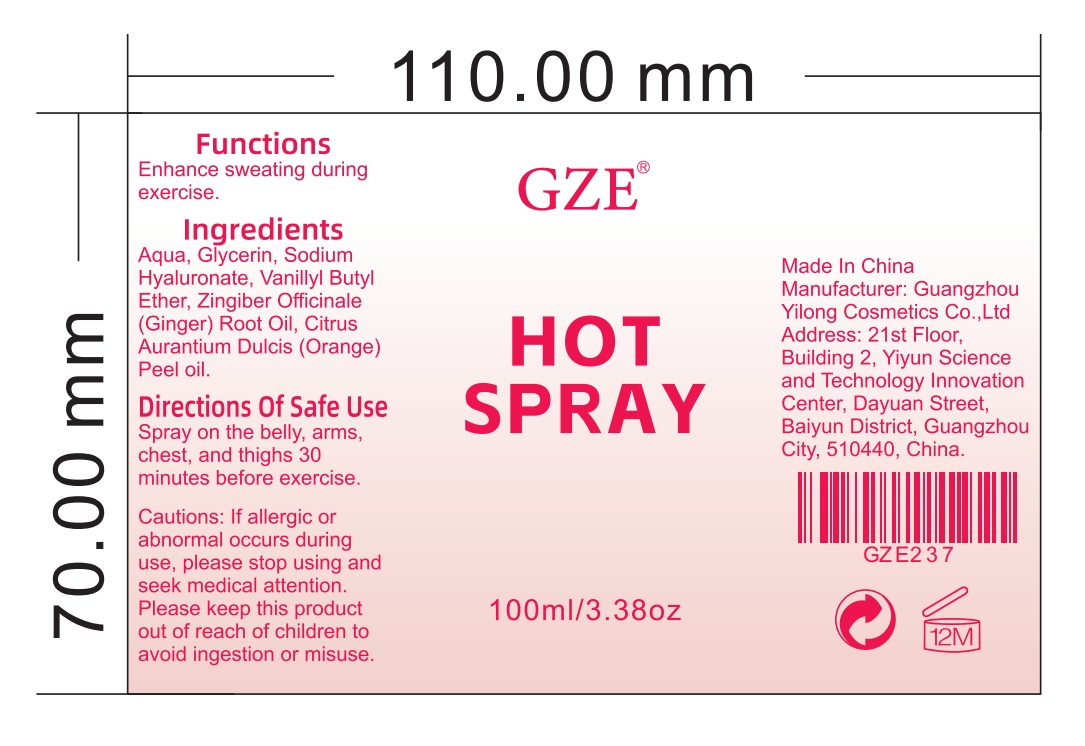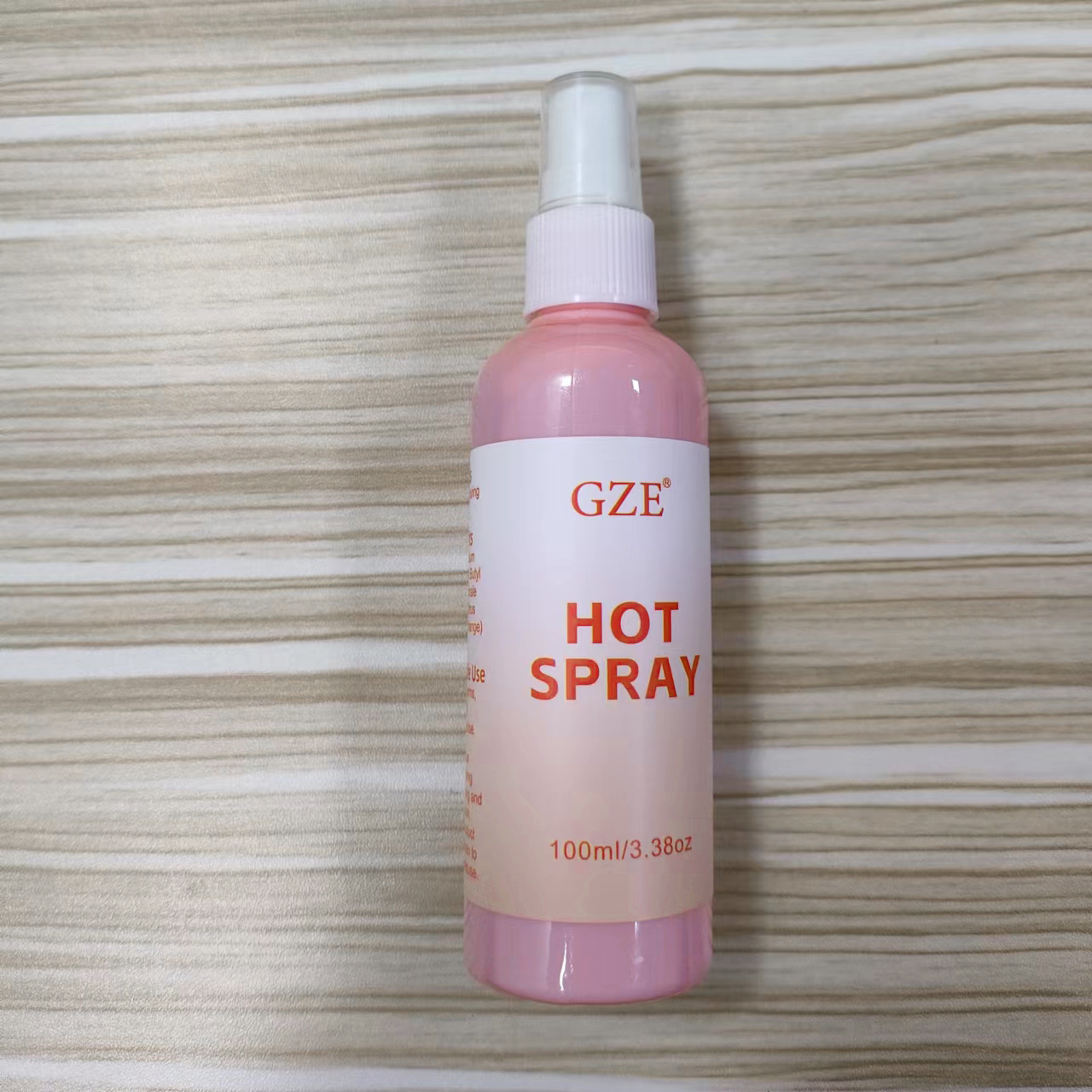 DRUG LABEL: Gze Hot Spary
NDC: 83566-237 | Form: SPRAY
Manufacturer: Guangzhou Yilong Cosmetics Co., Ltd
Category: otc | Type: HUMAN OTC DRUG LABEL
Date: 20240703

ACTIVE INGREDIENTS: GINGER OIL 5 g/100 mL; VANILLYL BUTYL ETHER 8.3 g/100 mL; ORANGE OIL 5 g/100 mL
INACTIVE INGREDIENTS: WATER; PEG-9 DIGLYCIDYL ETHER/SODIUM HYALURONATE CROSSPOLYMER; GLYCERIN

Gze Hot Spary

ACTIVE INGREDIENT

Vanillyl Butyl Ether

Zingiber Officinale (Ginger) Root Oil

Citrus Aurantium Dulcis (Orange) Peel oil

INACTIVE INGREDIENT

Aqua, Glycerin, Sodium Hyaluronate

INDICATIONS AND USAGE

Enhance sweating during exercise.

DOSAGE AND ADMINISTRATION

Spray on the belly, arms, chest, and thighs 30 minutes before exercise.

WARNINGS

For external use only.

Stop use and ask a doctor if rash occurs.

Do not use on damaged or broken skin.

When using this product keep out of eyes. Rinse with water to remove.

Keep out of reach of children. If swallowed, get medical help or contact a Poison Control Center right away.

PURPOSE

Enhance sweating during exercise.